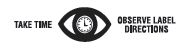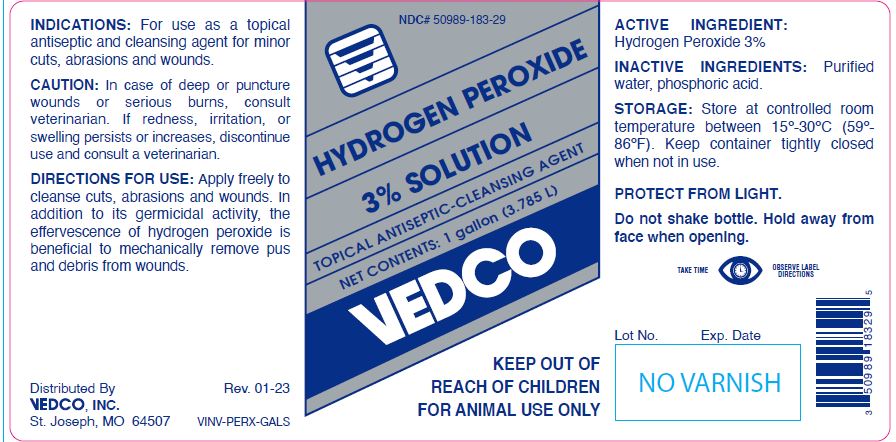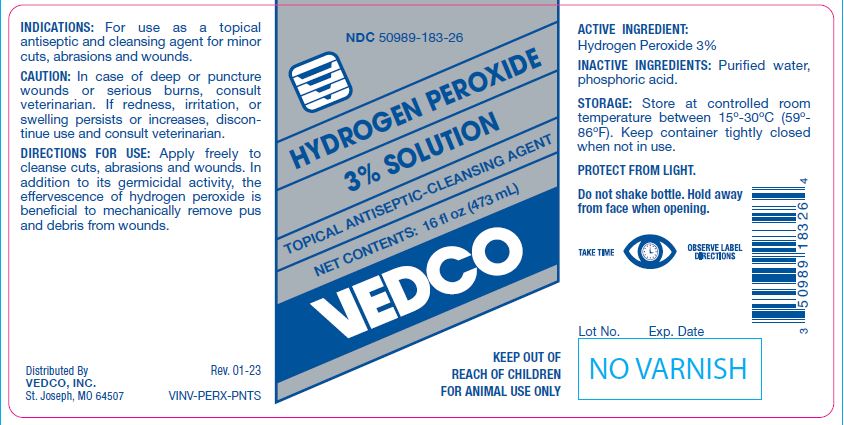 DRUG LABEL: Hydrogen Peroxide
NDC: 50989-183 | Form: SOLUTION
Manufacturer: Vedco, Inc.
Category: animal | Type: OTC ANIMAL DRUG LABEL
Date: 20250226

ACTIVE INGREDIENTS: HYDROGEN PEROXIDE 59.2 g/1 L

HYDROGEN PEROXIDE 3% SOLUTION

PURPOSE

TOPICAL ANTISEPTIC-CLEANSING AGENT

KEEP OUT OF REACH OF CHILDREN
FOR ANIMAL USE ONLY

INDICATIONS:

For use as a topical antiseptic and cleansing agent for minor cuts, abrasions and wounds.

CAUTION:

In case of deep or puncture wounds or serious burns, consult veterinarian. If redness, irritation, or swelling persists or increases, discontinue use and consult a veterinarian.

DIRECTIONS FOR USE:

Apply freely to cleanse cuts, abrasions and wounds. In addition to its germicidal activity, the effervescence of hydrogen peroxide is beneficial to mechanically remove pus and debris from wounds.

ACTIVE INGREDIENT:

Hydrogen Peroxide 3%

INACTIVE INGREDIENTS:

Purified water, phosphoric acid.

STORAGE:

Store at controlled room temperature between 15º-30ºC (59º- 86ºF). Protect from light. Keep container tightly closed when not in use.

PROTECT FROM LIGHT.
Do not shake bottle. Hold away from face when opening.

NET CONTENTS:

16 fl oz (473 mL) VINV-PERX-PNTS

1 gallon (3.785 L) VINV-PERX-GALS

INFORMATION FOR OWNERS/CAREGIVERS

Distributed By
VEDCO, INC.
St. Joseph, MO 64507